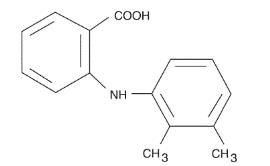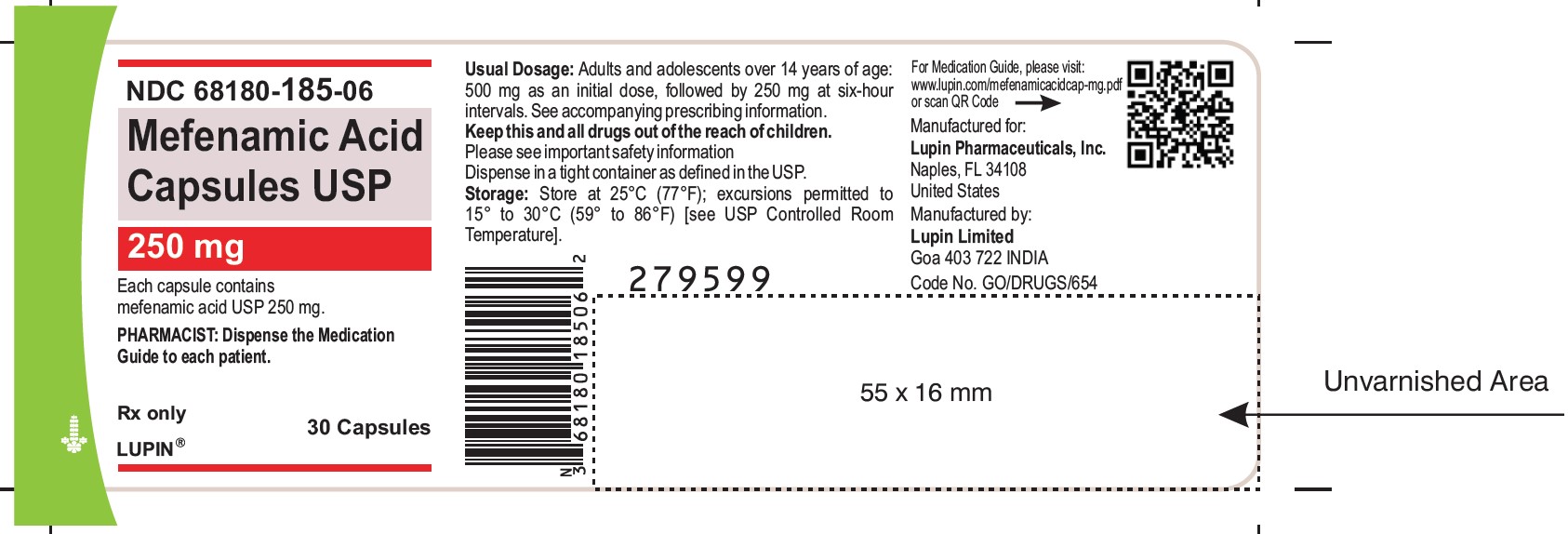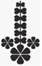 DRUG LABEL: Mefenamic Acid
NDC: 68180-185 | Form: CAPSULE
Manufacturer: Lupin Pharmaceuticals, Inc.
Category: prescription | Type: HUMAN PRESCRIPTION DRUG LABEL
Date: 20260204

ACTIVE INGREDIENTS: MEFENAMIC ACID 250 mg/1 1
INACTIVE INGREDIENTS: D&C YELLOW NO. 10; FD&C RED NO. 3; FD&C YELLOW NO. 6; FERROSOFERRIC OXIDE; GELATIN; LACTOSE MONOHYDRATE; MAGNESIUM STEARATE; POTASSIUM HYDROXIDE; PROPYLENE GLYCOL; SHELLAC; SODIUM LAURYL SULFATE; TITANIUM DIOXIDE

HIGHLIGHTS OF PRESCRIBING INFORMATION

These highlights do not include all the information needed to use MEFENAMIC ACID CAPSULES safely and effectively. See full prescribing information for MEFENAMIC ACID CAPSULES.
MEFENAMIC acid capsules, for oral use.
Initial U.S. Approval: 1967

WARNING: RISK OF SERIOUS CARDIOVASCULAR and GASTROINTESTINAL EVENTS

See full prescribing information for complete boxed warning.

Cardiovascular Thrombotic Events

- Nonsteroidal anti-inflammatory drugs (NSAIDs) cause an increased risk of serious cardiovascular thrombotic events, including myocardial infarction and stroke, which can be fatal. This risk may occur early in treatment and may increase with duration of use [see Warnings and Precautions (5.1)].
- Mefenamic acid is contraindicated in the setting of coronary artery bypass graft (CABG) surgery [see Warnings and Precautions (5.1)].

Gastrointestinal Bleeding, Ulceration, and Perforation

- NSAIDs cause an increased risk of serious gastrointestinal (GI) adverse events including bleeding, ulceration, and perforation of the stomach or intestines, which can be fatal. These events can occur at any time during use and without warning symptoms. Elderly patients and patients with a prior history of peptic ulcer disease and/or GI bleeding are at greater risk for serious GI events [see Warnings and Precautions (5.2)].

1 INDICATIONS AND USAGE

Mefenamic acid capsules are nonsteroidal anti-inflammatory drug indicated for:

- For management of mild to moderate pain in patient 14 years of age and older, when therapy will not exceed one week (7 days). (1.1)
- For treatment of primary dysmenorrhea. (1.2)

2 DOSAGE AND ADMINISTRATION

- Adults and adolescents 14 years of age and older: 500 mg given orally as an initial dose followed by 250 mg every 6 hours as needed (2.2)
- For the treatment of primary dysmenorrhea: 500 mg given orally as an initial dose followed by 250 mg every 6 hours (2.3)

3 DOSAGE FORMS AND STRENGTHS

- Capsule: 250 mg of mefenamic acid (3)

4 CONTRAINDICATIONS

- Known hypersensitivity (e.g., anaphylactic reactions and serious skin reactions) to mefenamic acid or any components of the drug product (4)
- History of asthma, urticaria, or other allergic-type reactions after taking aspirin or other NSAIDs. Severe, sometimes fatal, anaphylactic reactions to NSAIDs have been reported in such patients (4)
- In the setting of coronary artery bypass graft (CABG) surgery (4)

5 WARNINGS AND PRECAUTIONS

- Hepatotoxicity: Inform patients of warning signs and symptoms of hepatotoxicity. Discontinue if abnormal liver tests persist or worsen or if clinical signs and symptoms of liver disease develop. (5.3)
- Hypertension: Patients taking some antihypertensive medications may have impaired response to these therapies when taking NSAIDs. Monitor blood pressure. (5.4, 7)
- Heart Failureand Edema: Avoid use of mefenamic acid in patients with severe heart failure unless benefits are expected to outweigh risk of worsening heart failure. (5.5)
- Renal Toxicity: Monitor renal function in patients with renal or hepatic impairment, heart failure, dehydration, or hypovolemia. Avoid use of mefenamic acid in patients with advanced renal disease unless benefits are expected to outweigh risk of worsening renal function. (5.6)
- Anaphylactic Reactions: Seek emergency help if an anaphylactic reaction occurs. (5.7)
- Exacerbation of Asthma Related to Aspirin Sensitivity:Mefenamic acid is contraindicated in patients with aspirin-sensitive asthma. Monitor patients with preexisting asthma (without aspirin sensitivity). (5.8)
- Serious Skin Reactions: Discontinue mefenamic acid at first appearance of skin rash or other signs of hypersensitivity. (5.9)
- Drug Reaction with Eosinophiliaand Systemic Symptoms (DRESS): Discontinue and evaluate clinically. (5.10)
- Fetal Toxicity: Limit use of NSAIDs, including mefenamic acid, between about 20 to 30 weeks in pregnancy due to the risk of oligohydramnios/fetal renal dysfunction. Avoid use of NSAIDs in women at about 30 weeks gestation and later in pregnancy due to the risks of oligohydramnios/fetal renal dysfunction and premature closure of the fetal ductus arteriosus. (5.11, 8.1)
- Hematologic Toxicity: Monitor hemoglobin or hematocrit in patients with any signs or symptoms of anemia. (5.12, 7)

6 ADVERSE REACTIONS

In patients taking mefenamic acid or other NSAIDs, the most frequently reported adverse reactions occurring in approximately 1 to 10 % of patients are: abdominal pain, constipation, diarrhea, dyspepsia, flatulence, gross bleeding/perforation, heartburn, nausea, GI ulcers (gastric/duodenal), vomiting, abnormal renal function, anemia, dizziness, edema, elevated liver enzymes, headaches, increased bleeding time, pruritus, rashes, tinnitus (6.1)

To report SUSPECTED ADVERSE REACTIONS, contact Lupin Pharmaceuticals, Inc. at 1-800 399-2561 or FDA at 1-800-FDA-1088 or www.fda.gov/medwatch.

8 USE IN SPECIFIC POPULATIONS

Infertility: NSAIDs are associated with reversible infertility. Consider withdrawal of mefenamic acid in women who have difficulty conceiving. (8.3)

FULL PRESCRIBING INFORMATION

WARNING: RISK OF SERIOUS CARDIOVASCULAR and GASTROINTESTINAL EVENTS

Cardiovascular Thrombotic Events

- Nonsteroidal anti-inflammatory drugs (NSAIDs) cause an increased risk of serious cardiovascular thrombotic events, including myocardial infarction and stroke, which can be fatal. This risk may occur early in treatment and may increase with duration of use [see Warnings and Precautions (5.1)].
- Mefenamic acid is contraindicated in the setting of coronary artery bypass graft (CABG) surgery [see Contraindications (4), see Warnings and Precautions (5.1)].

Gastrointestinal Bleeding, Ulceration, and Perforation

- NSAIDs cause an increased risk of serious gastrointestinal (GI) adverse events including bleeding, ulceration, and perforation of the stomach or intestines, which can be fatal. These events can occur at any time during use and without warning symptoms. Elderly patients and patients with a prior history of peptic ulcer disease and/or GI bleeding are at greater risk for serious GI events [see Warnings and Precautions (5.2)].

1 INDICATIONS AND USAGE

1.1 Mild to Moderate Pain

Mefenamic acid capsules are indicated for management of mild to moderate pain in adults and pediatric patients 14 years of age and older, when therapy will not exceed one week (7 days).

1.2 Dysmenorrhea

Mefenamic acid capsules are indicated for treatment of primary dysmenorrhea.

2 DOSAGE AND ADMINISTRATION

2.1 Important Dosage and Administration Information

Carefully consider the potential benefits and risks of mefenamic acid capsules and other treatment options before deciding to use mefenamic acid capsules. Use the lowest effective dose for the shortest duration consistent with individual patient treatment goals [see Warnings and Precautions (5.2)].

After observing the response to initial therapy with mefenamic acid capsules, the dose and frequency should be adjusted to suit an individual patient's needs.

2.2 For the Management of Mild to Moderate Pain

The recommended dosage in adults and pediatric patients 14 years of age and older is 500 mg given orally as an initial dose followed by 250 mg every 6 hours as needed.

2.3 Dysmenorrhea

The recommended dose is 500 mg given orally as an initial dose followed by 250 mg every 6 hours starting with the onset of bleeding and associated symptoms.

3 DOSAGE FORMS AND STRENGTHS

250 mg size '1' capsules having ivory cap and ivory body imprinted with "LU" on cap and "R31" on body in black ink

4 CONTRAINDICATIONS

Mefenamic acid capsules are contraindicated in the following patients:

- Known hypersensitivity (e.g., anaphylactic reactions and serious skin reactions) to mefenamic acid or any components of the drug product [see Warnings and Precautions (5.7)].
- History of asthma, urticaria, or other allergic-type reactions after taking aspirin or other NSAIDs. Severe, sometimes fatal, anaphylactic reactions to NSAIDs have been reported in such patients [see Warnings and Precautions (5.7, 5.8, 5.9)].
- In the setting of coronary artery bypass graft (CABG) surgery [see Warnings and Precautions (5.1)].

5 WARNINGS AND PRECAUTIONS

5.1 Cardiovascular Thrombotic Events

Clinical trials of several COX-2 selective and nonselective NSAIDs of up to three years duration have shown an increased risk of serious cardiovascular (CV) thrombotic events, including myocardial infarction (MI) and stroke, which can be fatal. Based on available data, it is unclear that the risk for CV thrombotic events is similar for all NSAIDs. The relative increase in serious CV thrombotic events over baseline conferred by NSAID use appears to be similar in those with and without known CV disease or risk factors for CV disease. However, patients with known CV disease or risk factors had a higher absolute incidence of excess serious CV thrombotic events, due to their increased baseline rate. Some observational studies found that this increased risk of serious CV thrombotic events began as early as the first weeks of treatment. The increase in CV thrombotic risk has been observed most consistently at higher doses.

To minimize the potential risk for an adverse CV event in NSAID-treated patients, use the lowest effective dose for the shortest duration possible. Physicians and patients should remain alert for the development of such events throughout the entire treatment course, even in the absence of previous CV symptoms. Patients should be informed about the symptoms of serious CV events and the steps to take if they occur.

There is no consistent evidence that concurrent use of aspirin mitigates the increased risk of serious CV thrombotic events associated with NSAID use. The concurrent use of aspirin and an NSAID, such as mefenamic acid, increases the risk of serious gastrointestinal (GI) events [see Warnings and Precautions (5.2)].

Status Post Coronary Artery Bypass Graft (CABG) Surgery

Two large, controlled, clinical trials of a COX-2 selective NSAID for the treatment of pain in the first 10 to 14 days following CABG surgery found an increased incidence of myocardial infarction and stroke. NSAIDs are contraindicated in the setting of CABG [see Contraindications (4)].

Post-MI Patients

Observational studies conducted in the Danish National Registry have demonstrated that patients treated with NSAIDs in the post-MI period were at increased risk of reinfarction, CV-related death, and all-cause mortality beginning in the first week of treatment. In this same cohort, the incidence of death in the first year post-MI was 20 per 100 person years in NSAID-treated patients compared to 12 per 100 person years in non-NSAID exposed patients. Although the absolute rate of death declined somewhat after the first year post-MI, the increased relative risk of death in NSAID users persisted over at least the next four years of follow-up.

Avoid the use of mefenamic acid capsules in patients with a recent MI unless the benefits are expected to outweigh the risk of recurrent CV thrombotic events. If mefenamic acid is used in patients with a recent MI, monitor patients for signs of cardiac ischemia.

5.2 Gastrointestinal Bleeding, Ulceration, and Perforation

NSAIDs, including mefenamic acid, cause serious gastrointestinal (GI) adverse events including inflammation, bleeding, ulceration, and perforation of the esophagus, stomach, small intestine, or large intestine, which can be fatal. These serious adverse events can occur at any time, with or without warning symptoms, in patients treated with NSAIDs. Only one in five patients who develop a serious upper GI adverse event on NSAID therapy is symptomatic. Upper GI ulcers, gross bleeding, or perforation caused by NSAIDs occur in approximately 1 % of patients treated for 3 to 6 months, and in about 2 to 4 % of patients treated for one year. However, even short-term NSAID therapy is not without risk.

Risk Factors for GI Bleeding, Ulceration, and Perforation

Patients with a prior history of peptic ulcer disease and/or GI bleeding who used NSAIDs had a greater than 10- fold increased risk for developing a GI bleed compared to patients without these risk factors. Other factors that increase the risk for GI bleeding in patients treated with NSAIDs include longer duration of NSAID therapy, concomitant use of oral corticosteroids, anti-platelet drugs (such as aspirin), anticoagulants, or selective serotonin reuptake inhibitors (SSRIs), smoking, use of alcohol, older age, and poor general health status. Most postmarketing reports of fatal GI events occurred in elderly or debilitated patients. Additionally, patients with advanced liver disease and/or coagulopathy are at increased risk for GI bleeding.

Strategies to Minimize the GI Risks in NSAID-treated patients:

- Use the lowest effective dosage for the shortest possible duration.
- Avoid administration of more than one NSAID at a time.
- Avoid use in patients at higher risk unless benefits are expected to outweigh the increased risk of bleeding. For such patients, as well as those with active GI bleeding, consider alternate therapies other than NSAIDs.
- Remain alert for signs and symptoms of GI ulceration and bleeding during NSAID therapy.
- If a serious GI adverse event is suspected, promptly initiate evaluation and treatment, and discontinue mefenamic acid until a serious GI adverse event is ruled out.
- In the setting of concomitant use of low-dose aspirin for cardiac prophylaxis, monitor patients more closely for evidence of GI bleeding [see Drug Interactions (7.1)].

5.3 Hepatotoxicity

Elevations of ALT or AST (three or more times the upper limit of normal [ULN]) have been reported in approximately 1 % of NSAID-treated patients in clinical trials. In addition, rare, sometimes fatal, cases of severe hepatic injury, including fulminant hepatitis, liver necrosis, and hepatic failure have been reported.

Elevations of ALT or AST (less than three times ULN) may occur in up to 15 % of patients treated with NSAIDs including mefenamic acid.

Inform patients of the warning signs and symptoms of hepatotoxicity (e.g., nausea, fatigue, lethargy, diarrhea, pruritus, jaundice, right upper quadrant tenderness, and "flu-like" symptoms). If clinical signs and symptoms consistent with liver disease develop, or if systemic manifestations occur (e.g., eosinophilia, rash, etc.), discontinue mefenamic acid capsules immediately, and perform a clinical evaluation of the patient.

5.4 Hypertension

NSAIDs, including mefenamic acid, can lead to new onset of hypertension or worsening of pre- existing hypertension, either of which may contribute to the increased incidence of CV events. Patients taking angiotensin converting enzyme (ACE) inhibitors, thiazides diuretics, or loop diuretics may have impaired response to these therapies when taking NSAIDs [see Drug Interactions (7.1)].

Monitor blood pressure (BP) during the initiation of NSAID treatment and throughout the course of therapy.

5.5 Heart Failure and Edema

The Coxib and traditional NSAID Trialists' Collaboration meta-analysis of randomized controlled trials demonstrated an approximately two-fold increase in hospitalizations for heart failure in COX-2 selective-treated patients and non-selective NSAID-treated patients compared to placebo-treated patients. In a Danish National Registry study of patients with heart failure, NSAID use increased the risk of MI, hospitalization for heart failure, and death. Additionally, fluid retention and edema have been observed in some patients treated with NSAIDs. Use of mefenamic acid may blunt the CV effects of several therapeutic agents used to treat these medical conditions (e.g., diuretics, ACE inhibitors, or angiotensin receptor blockers [ARBs]) [see Drug Interactions (7.1)].

Avoid the use of mefenamic acid in patients with severe heart failure unless the benefits are expected to outweigh the risk of worsening heart failure. If mefenamic acid capsules are used in patients with severe heart failure, monitor patients for signs of worsening heart failure.

5.6 Renal Toxicity and Hyperkalemia

Renal Toxicity

Long-term administration of NSAIDs, including mefenamic acid, has resulted in renal papillary necrosis and other renal injury.

Renal toxicity has also been seen in patients in whom renal prostaglandins have a compensatory role in the maintenance of renal perfusion. In these patients, administration of an NSAID may cause a dose-dependent reduction in prostaglandin formation and, secondarily, in renal blood flow, which may precipitate overt renal decompensation. Patients at greatest risk of this reaction are those with impaired renal function, dehydration, hypovolemia, heart failure, liver dysfunction, those taking diuretics and ACE inhibitors or ARBs, and the elderly. Discontinuation of NSAID therapy is usually followed by recovery to the pretreatment state.

No information is available from controlled clinical studies regarding the use of mefenamic acid in patients with advanced renal disease. The renal effects of mefenamic acid may hasten the progression of renal dysfunction in patients with pre-existing renal disease.

Correct volume status in dehydrated or hypovolemic patients prior to initiating mefenamic acid. Monitor renal function in patients with renal or hepatic impairment, heart failure, dehydration, or hypovolemia during use of mefenamic acid [see Drug Interactions (7.1)]. Avoid the use of mefenamic acid in patients with advanced renal disease unless the benefits are expected to outweigh the risk of worsening renal function. If mefenamic acid is used in patients with advanced renal disease, monitor patients for signs of worsening renal function.

Hyperkalemia

Increases in serum potassium concentration, including hyperkalemia, have been reported with use of NSAIDs, even in some patients without renal impairment. In patients with normal renal function, these effects have been attributed to a hyporeninemic-hypoaldosteronism state.

5.7 Anaphylactic Reactions

Mefenamic acid has been associated with anaphylactic reactions in patients with and without known hypersensitivity to mefenamic acid and in patients with aspirin-sensitive asthma [see Contraindications (4); Warnings and Precautions (5.7)].

Advise patients to seek emergency help if anaphylactic reaction occurs.

5.8 Exacerbation of Asthma Related to Aspirin Sensitivity

A subpopulation of patients with asthma may have aspirin-sensitive asthma which may include chronic rhinosinusitis complicated by nasal polyps; severe, potentially fatal bronchospasm; and/or intolerance to aspirin and other NSAIDs. Because cross-reactivity between aspirin and other NSAIDs has been reported in such aspirin-sensitive patients, mefenamic acid is contraindicated in patients with this form of aspirin sensitivity [see Contraindications (4)]. When mefenamic acid is used in patients with pre-existing asthma (without known aspirin sensitivity), monitor patients for changes in the signs and symptoms of asthma.

5.9 Serious Skin Reactions

NSAIDs, including mefenamic acid, can cause serious skin adverse reactions such as exfoliative dermatitis, Stevens-Johnson Syndrome (SJS), and toxic epidermal necrolysis (TEN), which can be fatal. NSAIDs can also cause fixed drug eruption (FDE). FDE may present as a more severe variant known as generalized bullous fixed drug eruption (GBFDE), which can be life-threatening. These serious events may occur without warning.

Inform patients about the signs and symptoms of serious skin reactions and to discontinue the use of mefenamic acid capsules at the first appearance of skin rash or any other sign of hypersensitivity. Mefenamic acid is contraindicated in patients with previous serious skin reactions to NSAIDs [see Contraindications (4)].

5.10 Drug Reaction with Eosinophilia and Systemic Symptoms (DRESS)

Drug Reaction with Eosinophilia and Systemic Symptoms (DRESS) has been reported in patients taking NSAIDs such as mefenamic acid. Some of these events have been fatal or life-threatening. DRESS typically, although not exclusively, presents with fever, rash, lymphadenopathy, and/or facial swelling. Other clinical manifestations may include hepatitis, nephritis, hematological abnormalities, myocarditis, or myositis.

Sometimes symptoms of DRESS may resemble an acute viral infection. Eosinophilia is often present. Because this disorder is variable in its presentation, other organ systems not noted here may be involved. It is important to note that early manifestations of hypersensitivity, such as fever or lymphadenopathy, may be present even though rash is not evident. If such signs or symptoms are present, discontinue mefenamic acid and evaluate the patient immediately.

5.11 Fetal Toxicity

Premature Closure of Fetal Ductus Arteriosus:

Avoid use of NSAIDs, including mefenamic acid, in pregnant women at about 30 weeks gestation and later. NSAIDs, including mefenamic acid, increase the risk of premature closure of the fetal ductus arteriosus at approximately this gestational age.

Oligohydramnios/Neonatal Renal Impairment:

Use of NSAIDs, including mefenamic acid, at about 20 weeks gestation or later in pregnancy may cause fetal renal dysfunction leading to oligohydramnios and, in some cases, neonatal renal impairment. These adverse outcomes are seen, on average, after days to weeks of treatment, although oligohydramnios has been infrequently reported as soon as 48 hours after NSAID initiation. Oligohydramnios is often, but not always, reversible with treatment discontinuation. Complications of prolonged oligohydramnios may, for example, include limb contractures and delayed lung maturation. In some postmarketing cases of impaired neonatal renal function, invasive procedures such as exchange transfusion or dialysis were required.

If NSAID treatment is necessary between about 20 weeks and 30 weeks gestation, limit mefenamic acid use to the lowest effective dose and shortest duration possible. Consider ultrasound monitoring of amniotic fluid if mefenamic acid treatment extends beyond 48 hours. Discontinue mefenamic acid if oligohydramnios occurs and follow up according to clinical practice [see Use in Specific Populations (8.1)].

5.12 Hematological Toxicity

Anemia has occurred in NSAID-treated patients. This may be due to occult or gross blood loss, fluid retention, or an incompletely described effect on erythropoiesis. If a patient treated with mefenamic acid capsules has any signs or symptoms of anemia, monitor hemoglobin or hematocrit.

NSAIDs, including mefenamic acid, may increase the risk of bleeding events. Co-morbid conditions such as coagulation disorders or concomitant use of warfarin, other anticoagulants, antiplatelet agents (e.g., aspirin), serotonin reuptake inhibitors (SSRIs) and serotonin norepinephrine reuptake inhibitors (SNRIs) may increase this risk. Monitor these patients for signs of bleeding [see Drug Interactions (7.1)].

5.13 Masking of Inflammation and Fever

The pharmacological activity of mefenamic acid in reducing inflammation, and possibly fever, may diminish the utility of diagnostic signs in detecting infections.

5.14 Laboratory Monitoring

Because serious GI bleeding, hepatotoxicity, and renal injury can occur without warning symptoms or signs, consider monitoring patients on long-term NSAID treatment with a CBC and a chemistry profile checked periodically [see Warnings and Precautions (5.2, 5.3, 5.6)].

6 ADVERSE REACTIONS

The following adverse reactions are discussed in greater detail in other sections of the labeling:

- Cardiovascular Thrombotic Events [see Warnings and Precautions (5.1)]
- GI Bleeding, Ulceration and Perforation [see Warnings and Precautions (5.2)]
- Hepatotoxicity [see Warnings and Precautions (5.3)]
- Hypertension [see Warnings and Precautions (5.4)]
- Heart Failure and Edema [see Warnings and Precautions (5.5)]
- Renal Toxicity and Hyperkalemia [see Warnings and Precautions (5.6)]
- Anaphylactic Reactions [see Warnings and Precautions (5.7)]
- Serious Skin Reactions [see Warnings and Precautions (5.9, 5.10)]
- Hematologic Toxicity [see Warnings and Precautions (5.12)]

Because clinical trials are conducted under widely varying conditions, adverse reaction rates observed in the clinical trials of a drug cannot be directly compared to rates in the clinical trials of another drug and may not reflect the rates observed in practice.

The following adverse reactions associated with the use of mefenamic acid were identified in clinical studies or post- marketing reports. Because some of these reactions were reported voluntarily from a population of uncertain size, it is not always possible to reliably estimate their frequency or establish a causal relationship to drug exposure

In patients taking mefenamic acid or other NSAIDs, the most frequently reported adverse reactions occurring in approximately 1 to10 % of patients are:

Gastrointestinal - Abdominal pain, constipation, diarrhea, dyspepsia, flatulence, gross bleeding/perforation, heartburn, nausea, GI ulcers (gastric/duodenal), vomiting

Auditory System - Tinnitus

Genitourinary System - Abnormal renal function

Hepatic System - Elevated liver enzymes

Dermatologic - Pruritus, rashes

Cardiovascular - Anemia, edema

Central Nervous System - Dizziness, headache

Hematopoetic and lymphatic system - Increased bleeding time

Additional adverse experiences reported less frequently and listed here by body system include: General - anaphylactoid reactions, appetite changes, death, fever, infection, sepsis

Cardiovascular - congestive heart failure, hypertension, tachycardia, syncope arrhythmia, hypotension, myocardial infarction, palpitations, vasculitis

Gastrointestinal system - dry mouth, esophagitis, gastric/peptic ulcers, gastritis, gastrointestinal bleeding, glossitis, hematemesis, hepatitis, jaundice, eructation, liver failure, pancreatitis

Hematopoetic and lymphatic system - ecchymosis, eosinophilia, leukopenia, melena, purpura, rectal bleeding, stomatitis, thrombocytopenia, agranulocytosis, hemolytic anemia, aplastic anemia, lymph-adenopathy, pancytopenia

Metabolic - weight changes, hyperglycemia

Central Nervous System - anxiety, asthenia, confusion, depression, dream abnormalities, drowsiness; insomnia, malaise, nervousness, paresthesia, somnolence, tremors, vertigo, convulsions, coma, hallucinations, meningitis

Respiratory system - asthma, dyspnea, respiratory depression, pneumonia

Dermatologic - alopecia, photosensitivity, pruritus, sweat, angioedema, toxic epidermal necrosis, erythema multiforme, exfoliative dermatitis, Stevens-Johnson syndrome, fixed drug eruption (FDE), urticaria

Special senses - blurred vision, conjunctivitis, hearing impairment

Genitourinary system - cystitis, dysuria, hematuria, interstitial nephritis, oliguria/polyuria, proteinuria, renal failure

7 DRUG INTERACTIONS

7.1 Drug Interactions

See Table 1 for clinically significant drug interactions with mefenamic acid.

Table1: Clinically Significant Drug Interactions with Mefenamic Acid
Drugs That Interfere with Hemostasis
Clinical Impact: |  | - Mefenamic acid and anticoagulants such as warfarin have a synergistic effect on bleeding. The concomitant use of mefenamic acid and anticoagulants have an increased risk of serious bleeding compared to the use of either drug alone. - Serotonin release by platelets plays an important role in hemostasis. Case-control and cohort epidemiological studies showed that concomitant use of drugs that interfere with serotonin reuptake and an NSAID may potentiate the risk of bleeding more than an NSAID alone.
Intervention: |  | Monitor patients with concomitant use of mefenamic acid with anticoagulants (e.g., warfarin), antiplatelet agents (e.g., aspirin), selective serotonin reuptake inhibitors (SSRIs), and serotonin norepinephrine reuptake inhibitors (SNRIs) for signs of bleeding [see Warnings and Precautions (5.12)] .
Aspirin
Clinical Impact: |  | Controlled clinical studies showed that the concomitant use of NSAIDs and analgesic doses of aspirin does not produce any greater therapeutic effect than the use of NSAIDs alone. In a clinical study, the concomitant use of an NSAID and aspirin was associated with a significantly increased incidence of GI adverse reactions as compared to use of the NSAID alone [see Warnings and Precautions (5.2)] .
Intervention: |  | Concomitant use of mefenamic acid and analgesic doses of aspirin is not generally recommended because of the increased risk of bleeding [see Warnings and Precautions (5.12)] . Mefenamic acid is not a substitute for low dose aspirin for cardiovascular protection.
ACE Inhibitors, Angiotensin Receptor Blockers, and Beta-Blockers
Clinical Impact: |  | - NSAIDs may diminish the antihypertensive effect of angiotensin converting enzyme (ACE) inhibitors, angiotensin receptor blockers (ARBs), or beta-blockers (including propranolol). - In patients who are elderly, volume-depleted (including those on diuretic therapy), or have renal impairment, co-administration of an NSAID with ACE inhibitors or ARBs may result in deterioration of renal function, including possible acute renal failure. These effects are usually reversible.
Intervention: |  | - During concomitant use of mefenamic acid and ACE-inhibitors, ARBs, or beta-blockers, monitor blood pressure to ensure that the desired blood pressure is obtained. - During concomitant use of mefenamic acid and ACE-inhibitors or ARBs in patients who are elderly, volume-depleted, or have impaired renal function, monitor for signs of worsening renal function [see Warnings and Precautions (5.6)]. - When these drugs are administered concomitantly, patients should be adequately hydrated. Assess renal function at the beginning of the concomitant treatment and periodically thereafter.
Diuretics
Clinical Impact: | Clinical studies, as well as post-marketing observations, showed that NSAIDs reduced the natriuretic effect of loop diuretics (e.g., furosemide) and thiazide diuretics in some patients. This effect has been attributed to the NSAID inhibition of renal prostaglandin synthesis.
Intervention: | During concomitant use of mefenamic acid with diuretics, observe patients for signs of worsening renal function, in addition to assuring diuretic efficacy including antihypertensive effects [see Warnings and Precautions (5.6)] .
Digoxin
Clinical Impact: | The concomitant use of mefenamic acid with digoxin has been reported to increase the serum concentration and prolong the half-life of digoxin.
Intervention: | During concomitant use of mefenamic acid and digoxin, monitor serum digoxin levels.
Lithium
Clinical Impact: | NSAIDs have produced elevations in plasma lithium levels and reductions in renal lithium clearance. This effect has been attributed to NSAID inhibition of renal prostaglandin synthesis [See Clinical Pharmacology (12.3)] .
Intervention: | During concomitant use of mefenamic acid and lithium, monitor patients for signs of lithium toxicity.
Methotrexate
Clinical Impact: | Concomitant use of NSAIDs and methotrexate may increase the risk for methotrexate toxicity (e.g., neutropenia, thrombocytopenia, renal dysfunction).
Intervention: | During concomitant use of mefenamic acid and methotrexate, monitor patients for methotrexate toxicity.
Cyclosporine
Clinical Impact: | Concomitant use of mefenamic acid and cyclosporine may increase cyclosporine's nephrotoxicity.
Intervention: | During concomitant use of mefenamic acid and cyclosporine, monitor patients for signs of worsening renal function.
NSAIDs and Salicylates
Clinical Impact: | Concomitant use of mefenamic acid with other NSAIDs or salicylates (e.g., diflunisal, salsalate) increases the risk of GI toxicity, with little or no increase in efficacy [see Warnings and Precautions (5.2)] .
Intervention: | The concomitant use of mefenamic acid with other NSAIDs or salicylates is not recommended.
Pemetrexed
Clinical Impact: | Concomitant use of mefenamic acid and pemetrexed may increase the risk of pemetrexed- associated myelosuppression, renal, and GI toxicity (see the pemetrexed prescribing information).
Intervention: | During concomitant use of mefenamic acid and pemetrexed, in patients with renal impairment whose creatinine clearance ranges from 45 to 79 mL/min, monitor for myelosuppression, renal and GI toxicity. NSAIDs with short elimination half-lives (e.g., diclofenac, indomethacin) should be avoided for a period of two days before, the day of, and two days following administration of pemetrexed. In the absence of data regarding potential interaction between pemetrexed and NSAIDs with longer half-lives (e.g., meloxicam, nabumetone), patients taking these NSAIDs should interrupt dosing for at least five days before, the day of, and two days following pemetrexed administration.
Antacid
Clinical Impact: |  |  | Concomitant ingestion of antacids containing magnesium hydroxide has been shown to significantly increase the rate and extent of mefenamic acid absorption [See Clinical Pharmacology (12.3)]
Intervention: |  |  | Concomitant use of mefenamic acid and antacids is not generally recommended because of possible increased adverse events.

Drug/Laboratory Test Interactions

Mefenamic acid may prolong prothrombin time. Therefore, when the drug is administered to patients receiving oral anticoagulant drugs, frequent monitoring of prothrombin time is necessary.

A false-positive reaction for urinary bile, using the diazo tablet test, may result after mefenamic acid administration. If biliuria is suspected, other diagnostic procedures, such as the Harrison spot test, should be performed.

8 USE IN SPECIFIC POPULATIONS

8.1 Pregnancy

Risk Summary

Use of NSAIDs, including mefenamic acid, can cause premature closure of the fetal ductus arteriosus and fetal renal dysfunction leading to oligohydramnios and, in some cases, neonatal renal impairment. Because of these risks, limit dose and duration of mefenamic acid use between about 20 and 30 weeks of gestation, and avoid mefenamic acid use at about 30 weeks of gestation and later in pregnancy (see Clinical Considerations, Data).

Premature Closure of Fetal Ductus Arteriosus

Use of NSAIDs, including mefenamic acid, at about 30 weeks gestation or later in pregnancy increases the risk of premature closure of the fetal ductus arteriosus.

Oligohydramnios/Neonatal Renal Impairment

Use of NSAIDs at about 20 weeks gestation or later in pregnancy has been associated with cases of fetal renal dysfunction leading to oligohydramnios, and in some cases, neonatal renal impairment.

Data from observational studies regarding other potential embryofetal risks of NSAID use in women in the first or second trimesters of pregnancy are inconclusive. In animal reproduction studies, administration of mefenamic acid to pregnant rats during organogenesis through lactation resulted in perinatal death and smaller litter sizes at exposures comparable to the Maximum Recommended Human Dose (MRHD) (see Data). Based on animal data, prostaglandins have been shown to have an important role in endometrial vascular permeability, blastocyst implantation, and decidualization. In animal studies, administration of prostaglandin synthesis inhibitors such as mefenamic acid, resulted in increased pre- and post-implantation loss. Prostaglandins also have been shown to have an important role in fetal kidney development. In published animal studies, prostaglandin synthesis inhibitors have been reported to impair kidney development when administered at clinically relevant doses.

The background risk of major birth defects and miscarriage for the indicated population(s) is unknown. All pregnancies have a background risk of birth defect, loss, or other adverse outcomes. In the U.S. general population, the estimated background risk of major birth defects and miscarriage in clinically recognized pregnancies is 2 % to 4 % and 15 % to 20 %, respectively.

Clinical Considerations

Fetal/Neonatal Adverse Reactions

Premature Closure of Fetal Ductus Arteriosus:

Avoid use of NSAIDs in women at about 30 weeks gestation and later in pregnancy, because NSAIDs, including mefenamic acid capsules, can cause premature closure of the fetal ductus arteriosus (see Data).

Oligohydramnios/Neonatal Renal Impairment:

If an NSAID is necessary at about 20 weeks gestation or later in pregnancy, limit the use to the lowest effective dose and shortest duration possible. If mefenamic acid treatment extends beyond 48 hours, consider monitoring with ultrasound for oligohydramnios. If oligohydramnios occurs, discontinue mefenamic acid capsules and follow up according to clinical practice (see Data).

Labor or Delivery

There are no studies on the effects of mefenamic acid during labor or delivery. In animal studies, NSAIDs, including mefenamic acid, inhibit prostaglandin synthesis, cause delayed parturition, and increase the incidence of stillbirth.

Data

Human Data

Premature Closure of Fetal Ductus Arteriosus:

Published literature reports that the use of NSAIDs at about 30 weeks of gestation and later in pregnancy may cause premature closure of the fetal ductus arteriosus.

Oligohydramnios/Neonatal Renal Impairment:

Published studies and postmarketing reports describe maternal NSAID use at about 20 weeks gestation or later in pregnancy associated with fetal renal dysfunction leading to oligohydramnios, and in some cases, neonatal renal impairment. These adverse outcomes are seen, on average, after days to weeks of treatment, although oligohydramnios has been infrequently reported as soon as 48 hours after NSAID initiation. In many cases, but not all, the decrease in amniotic fluid was transient and reversible with cessation of the drug. There have been a limited number of case reports of maternal NSAID use and neonatal renal dysfunction without oligohydramnios, some of which were irreversible. Some cases of such as exchange transfusion or dialysis.

Methodological limitations of these postmarketing studies and reports include lack of a control group; limited information regarding dose, duration, and timing of drug exposure; and concomitant use of other medications. These limitations preclude establishing a reliable estimate of the risk of adverse fetal and neonatal outcomes with maternal NSAID use. Because the published safety data on neonatal outcomes involved mostly preterm infants, the generalizability of certain reported risks to the full-term infant exposed to NSAIDs through maternal use is uncertain.

Animal Data

Pregnant rats administered 249 mg/kg of mefenamic acid (1.6-times the MRHD of 1500 mg/day on a mg/m^2 basis) from Gestation Day (GD) 6 to GD 15 did not result in any clear adverse developmental effects.

Pregnant rabbits given 50 mg/kg of mefenamic acid (0.6-times the MRHD on a mg/m^2 basis) from GD 6 to GD 18 did not result in any clear treatment-related adverse developmental effects. However, incidences of resorption were greater in treated compared to control animals. This dose was associated with some evidence of maternal toxicity with 4 of 18 rabbits exhibiting diarrhea and weight loss.

Dietary administration of mefenamic acid at a dose of 181 mg/kg (1.2-times the MRHD on a mg/m^2 basis) to pregnant rats from GD 15 to weaning resulted in an increased incidence of perinatal death. Treated dams were associated with decreased weight gain and delayed parturition. In another study, dietary administration of mefenamic acid at a dose of 155 mg/kg (equivalent to the MRHD of 1500 mg/day on a mg/m^2 basis) to females 15 days prior to mating through to weaning resulted in smaller average litter sizes and higher incidence of perinatal death.

8.2 Lactation

Risk Summary

Mefenamic acid is present in human milk in low amounts and may be transferred to breastfed infants. There are no available data on the effects of mefenamic acid on the breastfed infant or on milk production. The developmental and health benefits of breastfeeding should be considered along with the mother's clinical need for mefenamic acid and any potential adverse effects on the breastfed infant from the mefenamic acid or from the underlying maternal condition.

8.9 Females and Males of Reproductive Potential

Infertility

Females

Based on the mechanism of action, the use of prostaglandin-mediated NSAIDs, including mefenamic acid may delay or prevent rupture of ovarian follicles, which has been associated with reversible infertility in some women.

Small studies in women treated with NSAIDs have also shown a reversible delay in ovulation. Consider withdrawal of NSAIDs, including mefenamic acid, in women who have difficulties conceiving or who are undergoing investigation of infertility. Published animal studies have shown that administration of prostaglandin synthesis inhibitors has the potential to disrupt prostaglandin in mediated follicular rupture required for ovulation. Rats administered mefenamic acid resulted in decreased fertility [see Nonclinical Toxicology (13.1)].

8.4 Pediatric Use

The safety and effectiveness of mefenamic acid have been established for management of mild to moderate pain in pediatric patients 14 years of age and older.

The safety and effectiveness of mefenamic acid have been established for treatment of primary dysmenorrhea in pediatric patients.

The safety and effectiveness of mefenamic acid have not been established for management of mild to moderate pain in pediatric patients less than 14 years of age.

8.5 Geriatric Use

Elderly patients, compared to younger patients, are at greater risk for NSAID-associated serious cardiovascular, gastrointestinal, and/or renal adverse reactions. If the anticipated benefit for the elderly patient outweighs these potential risks, start dosing at the low end of the dosing range, and monitor patients for adverse effects [see Warnings and Precautions (5.1, 5.2, 5.3, 5.6, 5.14)].

Clinical studies of mefenamic acid did not include sufficient numbers of subjects aged 65 and over to determine whether they respond differently from younger subjects. As with any NSAID, caution should be exercised in treating the elderly (65 years and older).

Mefenamic acid is known to be substantially excreted by the kidney, and the risk of toxic reactions to this drug may be greater in patients with impaired renal function. Because elderly patients are more likely to have decreased renal function, care should be taken in dose selection, and it may be useful to monitor renal function [see Warnings and Precautions (5.1, 5.2, 5.3, 5.6, 5.14), Clinical Pharmacology (12.2), Adverse Reactions (7.1)].

8.6 Renal Impairment

The renal effects of mefenamic acid capsules may hasten the progression of renal dysfunction in patients with pre-existing renal disease.

Given that mefenamic acid, its metabolites and conjugates are primarily excreted by the kidneys, the potential exists for mefenamic acid metabolites to accumulate. Mefenamic acid capsules should not be administered to patients with pre-existing renal disease or in patients with significantly impaired renal function [see Warnings and Precautions (5.6)].

8.7 Hepatic Impairment

As hepatic metabolism is a significant pathway of mefenamic acid elimination, patients with acute and chronic hepatic disease may require reduced doses of mefenamic acid compared to patients with normal hepatic function [see Warnings and Precautions (5.3)].

10 OVERDOSAGE

Symptoms following acute NSAID overdosages have been typically limited to lethargy, drowsiness, nausea, vomiting, and epigastric pain, which have been generally reversible with supportive care. Gastrointestinal bleeding has occurred. Hypertension, acute renal failure, respiratory depression, and coma have occurred but were rare [see Warnings and Precautions (5.1, 5.2, 5.4, 5.6)].

Manage patients with symptomatic and supportive care following an NSAID overdosage. There are no specific antidotes. Consider emesis and/or activated charcoal (60 to 100 grams in adults, 1 to 2 grams per kg of body weight in pediatric patients) and/or osmotic cathartic in symptomatic patients seen within four hours of ingestion or in patients with a large overdose (5 to 10 times the recommended dosage). Forced diuresis, alkalinization of urine, hemodialysis, or hemoperfusion may not be useful due to high protein binding.

For additional information about overdosage treatment, contact a Poison Help Line (1-800-222-1222).

11 DESCRIPTION

Mefenamic acid capsules USP contains active moiety mefenamic acid, which is a member of the fenamate group of nonsteroidal anti-inflammatory drugs (NSAIDs). The chemical name of mefenamic acid is N-2,3-xylylanthranilic acid. The molecular weight is 241.29 g/mol. Its molecular formula is C15H15N02 and the structural formula of mefenamic acid is:

Mefenamic acid is a white to greyish-white, odorless, microcrystalline powder with a melting point of 230° to 231°C and water solubility of 0.004 % at pH 7.1.

Mefenamic acid capsules are for oral administration. Each capsule contains 250 mg of mefenamic acid, lactose monohydrate and magnesium stearate. The capsule shell contains gelatin, sodium lauryl sulfate, titanium dioxide, D&C yellow No. 10, FD&C yellow No. 6 and FD&C red No. 3.

12 CLINICAL PHARMACOLOGY

12.1 Mechanism of Action

Mefenamic acid has analgesic, anti-inflammatory, and antipyretic properties. The mechanism of action of mefenamic acid, like that of other NSAIDs, is not completely understood but involves inhibition of cyclooxygenase (COX-1 and COX-2).

Mefenamic acid is a potent inhibitor of prostaglandin synthesis in vitro. Mefenamic acid concentrations reached during therapy have produced in vivo effects. Prostaglandins sensitize afferent nerves and potentiate the action of bradykinin in inducing pain in animal models.

Prostaglandins are mediators of inflammation. Because mefenamic acid is an inhibitor of prostaglandin synthesis, its mode of action may be due to a decrease of prostaglandins in peripheral tissues.

12.3 Pharmacokinetics

Absorption

Mefenamic acid is rapidly absorbed after oral administration. In two 500-mg single oral dose studies, the mean extent of absorption was 30.5 mcg/hr/mL (17 %CV). The bioavailability of the capsule relative to an IV dose or an oral solution has not been studied.

Following a single 1-gram oral dose, mean peak plasma levels ranging from 10 to 20 mcg/mL have been reported. Peak plasma levels are attained in 2 to 4 hours. Following multiple doses, plasma levels are proportional to dose with no evidence of drug accumulation. In a multiple dose trial of normal adult subjects (n=6) receiving 1-gram doses of mefenamic acid four times daily, steady-state concentrations of 20 mcg/mL were reached on the second day of administration, consistent with the short half-life.

The effect of food on the rate and extent of absorption of mefenamic acid has not been studied.

Distribution

Mefenamic acid has been reported as being greater than 90 % bound to albumin. The relationship of unbound fraction to drug concentration has not been studied. The apparent volume of distribution (Vzss/F) estimated following a 500-mg oral dose of mefenamic acid was 1.06 L/kg.

Based on its physical and chemical properties, mefenamic acid is expected to be excreted in human breast milk [see Use in Specific Populations (8.2)].

Elimination

Metabolism

Mefenamic acid is metabolized by cytochrome P450 enzyme CYP2C9 to 3-hydroxymethyl mefenamic acid (Metabolite I). Further oxidation to a 3-carboxymefenamic acid (Metabolite II) may occur. The activity of these metabolites has not been studied. The metabolites may undergo glucuronidation and mefenamic acid is also glucuronidated directly. The mefenamic acid glucuronide may bind irreversibly to plasma proteins. A peak plasma level approximating 20 mcg/mL was observed at 3 hours for the hydroxy metabolite and its glucuronide (n=6) after a single 1-gram dose. Similarly, a peak plasma level of 8 mcg/mL was observed at 6 to 8 hours for the carboxy metabolite and its glucuronide.

Excretion

Approximately fifty-two percent of a mefenamic acid dose is excreted into the urine primarily as glucuronides of mefenamic acid (6 %), 3-hydroxymefenamic acid (25 %) and 3-carboxymefenamic acid (21 %). The fecal route of elimination accounts for up to 20 % of the dose, mainly in the form of unconjugated 3- carboxymefenamic acid.

The elimination half-life of mefenamic acid is approximately two hours. Half-lives of metabolites I and II have not been precisely reported but appear to be longer than the parent compound. The metabolites may accumulate in patients with renal or hepatic failure.

Table 2. Pharmacokinetic Parameter Estimates for Mefenamic Acid
PK Parameters | Normal Healthy Adults (18 to 45 yr)
 | Value | CV
Tmax (hr) | 2 | 66
Oral clearance (L/hr) | 21.23 | 38
Apparent volume of distribution; Vz/F (L/kg) | 1.06 | 60
Half-life; t½ (hrs) | 2 to 4 | N/A

Specific Populations

Race: Pharmacokinetic differences due to race have not been identified.

Hepatic Impairment: Mefenamic acid pharmacokinetics have not been studied in patients with hepatic dysfunction.

Renal Impairment: Mefenamic acid pharmacokinetics have not been investigated in subjects with renal insufficiency.

Drug Interaction Studies

Aspirin: When NSAIDs were administered with aspirin, the protein binding of NSAIDs were reduced, although the clearance of free NSAID was not altered. The clinical significance of this interaction is not known. See Table 1 for clinically significant drug interactions of NSAIDs with aspirin [see Drug Interactions (7.1)].

Antacid: In a single dose study (n=6), ingestion of an antacid containing 1.7-gram of magnesium hydroxide with 500-mg of mefenamic acid increased the Cmax and AUC of mefenamic acid by 125 % and 36 %, respectively.

Lithium: The mean minimum lithium concentration increased 15 %, and the renal clearance decreased by approximately 20 %.

13 NONCLINICAL TOXICOLOGY

13.1 Carcinogenesis, Mutagenesis, Impairment of Fertility

Carcinogenesis

Long-term studies in animals to evaluate the carcinogenic potential of mefenamic acid have not been conducted.

Mutagenesis

Studies to evaluate the mutagenic potential of mefenamic acid have not been completed.

Impairment of Fertility

Dietary administration of mefenamic acid to male rats 61 days- and to female rats 15 days- prior to mating through to Gestation Day (GD) 21 at a dose of 155 mg/kg/day (equivalent to the Maximum Recommended Human Dose [MRHD] of 1500 mg/day on a mg/m^2 basis) resulted in decreased corpora lutea.

In another study, rats administered up to 10-times a human dose of 250 mg showed decreased fertility.

14 CLINICAL STUDIES

14.1 Treatment of Primary Spasmodic Dysmenorrhea

In controlled, double-blind, clinical trials, mefenamic acid was evaluated for the treatment of primary spasmodic dysmenorrhea. The parameters used in determining efficacy included pain assessment by both patient and investigator; the need for concurrent analgesic medication; and evaluation of change in frequency and severity of symptoms characteristic of spasmodic dysmenorrhea. Patients received either mefenamic acid, 500 mg (2 capsules) as an initial dose of 250 mg every 6 hours, or placebo at onset of bleeding or of pain, whichever began first. After three menstrual cycles, patients were crossed over to the alternate treatment for an additional three cycles. Patients in the mefenamic acid group had statistically significantly better results compared to placebo on the efficacy parameters (pain assessment by both patient and investigator; the need for concurrent analgesic medication; and evaluation of change in frequency and severity of symptoms characteristic of spasmodic dysmenorrhea).

16 HOW SUPPLIED/STORAGE AND HANDLING

16.1 How Supplied

Mefenamic acid capsules USP, 250 mg are available as size '1' capsules having ivory cap and ivory body imprinted with "LU" on cap and "R31" on body in black ink, containing white to off white granular powder.

They are supplied as follows:

NDC 68180-185-06 Bottles of 30's

Dispense in a tight container as defined in the USP.

16.2 Storage and Handling

Store at 25°C (77°F); excursions permitted to 15° to 30°C (59° to 86°F) [see USP Controlled Room Temperature].

17 PATIENT COUNSELING INFORMATION

Advise the patient to read the FDA-approved patient labeling (Medication Guide) that accompanies each prescription dispensed. Inform patients, families and their caregivers of the following information before initiating therapy with mefenamic acid capsules and periodically during the course of ongoing therapy.

Cardiovascular Thrombotic Events

Advise patients to be alert for the symptoms of cardiovascular thrombotic events, including chest pain, shortness of breath, weakness, or slurring of speech, and to report any of these symptoms to their healthcare provider immediately [see Warnings and Precautions (5.1)].

Gastrointestinal Bleeding, Ulceration, and Perforation

Advise patients to report symptoms of ulcerations and bleeding, including epigastric pain, dyspepsia, melena, and hematemesis to their healthcare provider. In the setting of concomitant use of low-dose aspirin for cardiac prophylaxis, inform patients of the increased risk for and the signs and symptoms of GI bleeding [see Warnings and Precautions (5.2)].

Hepatotoxicity

Inform patients of the warning signs and symptoms of hepatotoxicity (e.g., nausea, fatigue, lethargy, pruritus, diarrhea, jaundice, right upper quadrant tenderness, and "flu-like" symptoms). If these occur, instruct patients to stop mefenamic acid capsules and seek immediate medical therapy [see Warnings and Precautions (5.3)].

Heart Failure and Edema

Advise patients to be alert for the symptoms of congestive heart failure including shortness of breath, unexplained weight gain, or edema and to contact their healthcare provider if such symptoms occur [see Warnings and Precautions (5.5)].

Anaphylactic Reactions

Inform patients of the signs of an anaphylactic reaction (e.g., difficulty breathing, swelling of the face or throat). Instruct patients to seek immediate emergency help if these occur [see Contraindications (4), Warnings and Precautions (5.7)].

Serious Skin Reactions, including DRESS

Advise patients to stop mefenamic acid capsules immediately if they develop any type of rash or fever and to contact their healthcare provider as soon as possible [see Warnings and Precautions (5.9)].

Female Fertility

Advise females of reproductive potential who desire pregnancy that NSAIDs, including mefenamic acid capsules, may be associated with a reversible delay in ovulation. [see Use in Specific Populations (8.3)].

Fetal Toxicity

Inform pregnant women to avoid use of mefenamic acid capsules and other NSAIDs starting at 30 weeks gestation because of the risk of the premature closing of the fetal ductus arteriosus. If treatment with mefenamic acid capsules is needed for a pregnant woman between about 20 to 30 weeks gestation, advise her that she may need to be monitored for oligohydramnios, if treatment continues for longer than 48 hours [see Warnings and Precautions (5.11), Use in Specific Populations (8.1)].

Avoid Concomitant Use of NSAIDs

Inform patients that the concomitant use of mefenamic acid capsules with other NSAIDs or salicylates (e.g., diflunisal, salsalate) is not recommended due to the increased risk of gastrointestinal toxicity, and little or no increase in efficacy [see Warnings and Precautions (5.2), Drug Interactions (7.1)]. Alert patients that NSAIDs may be present in "over the counter" medications for treatment of colds, fever, or insomnia.

Use of NSAIDs and Low-Dose Aspirin

Inform patients not to use low-dose aspirin concomitantly with mefenamic acid capsules until they talk to their healthcare provider [see Drug Interactions (7.1)].

LUPIN and the are registered trademarks of Lupin Pharmaceuticals, Inc.

Manufactured for:

Lupin Pharmaceuticals, Inc.

Naples, FL 34108

United States

Manufactured by:

Lupin Limited

Goa 403 722

INDIA

Revised: February 2026 ID: 282951

Medication Guide
Mefenamic (me-fe-NAM-ik) Acid Capsules USP

Mefenamic acid capsules are prescription medicine that contains mefenamic acid (a nonsteroidal anti-inflammatory drug [NSAID]).

What is the most important information I should know about mefenamic acid capsules, and medicines called nonsteroidal anti-inflammatory drugs (NSAIDs)?
Mefenamic acid capsules may cause serious side effects, including:

- Increased risk of a heart attack or stroke that can lead to death. This risk may happen early in treatment and may increase:
  - with increasing doses of NSAIDs
  - with longer use of NSAIDs

Do not take mefenamic acid capsules right before or after a heart surgery called a "coronary artery bypass graft (CABG)". Avoid taking mefenamic acid capsules after a recent heart attack unless your healthcare provider tells you to. You may have an increased risk of another heart attack if you take mefenamic acid capsules after a recent heart attack.

- Increased risk of bleeding, ulcers and tears (perforation) of the esophagus (tube leading from the mouth to the stomach), stomach and intestines:
  - anytime during use
  - without warning symptoms
  - that may cause death

The risk of getting an ulcer or bleeding increases with:
o past history of stomach ulcers, or stomach or intestinal bleeding with use of NSAIDs
o increasing doses of NSAIDs
o longer use of NSAIDs
o smoking
o drinking alcohol
o older age
o poor health
o advanced liver disease
o bleeding problems
Mefenamic acid capsules should only be used:
o exactly as prescribed
o at the lowest dose possible for your treatment
o for the shortest time needed

What are m efenamic acid capsules?
Mefenamic acid capsules are a prescription medicine used:

- for the management of mild to moderate pain in adults and children 14 years of age and older, when your treatment will not be longer than 1 week (7 days).
- for the treatment of menstrual cramps.

It is not known if mefenamic acid capsules are safe and effective for the management of mild to moderate pain in children less than 14 years of age.

Who should not take mefenamic acid capsules?
Do not take mefenamic acid capsules :

- if you are allergic to mefenamic acid or to any of the ingredients in mefenamic acid capsules. See the end of this Medication Guide for a complete of ingredients in mefenamic acid capsules.
- if you have had an asthma attack, hives, or other allergic reaction after taking aspirin or any other NSAIDs.
- right before or after heart bypass surgery.

Before taking mefenamic acid capsules, tell your healthcare provider about all of your medical conditions, including if you:

- have heart problems
- have bleeding problems
- have or have had ulcers
- have liver or kidney problems
- have high blood pressure
- have asthma
- are pregnant or plan to become pregnant. Taking mefenamic acid capsules at about 20 weeks of pregnancy or later may harm your unborn baby.

o If you need to take mefenamic acid capsules for more than 2 days when you are between 20 and 30 weeks of pregnancy, your healthcare provider may need to monitor the amount of fluid in your womb around your baby. You should not take mefenamic acid capsules after about 30 weeks of pregnancy.
o Mefenamic acid capsules may cause fertility problems in females, which may affect your ability to become pregnant. Talk to your healthcare provider if this is a concern for you.

- are breastfeeding or plan to breastfeed. Mefenamic acid can pass into your breast milk. Talk to your healthcare provider about the best way to feed your baby during treatment with mefenamic acid capsules.

Tell your healthcare provider about all of the medicines you take, including prescription or over-the-counter medicines, vitamins, or herbal supplements. Mefenamic acid capsules and some other medicines can interact with each other and cause serious side effects. Do not start taking any new medicine without talking to your healthcare provider first.

How should I take mefenamic acid capsules?

- Take mefenamic acid capsules exactly as your healthcare provider tells you to take it.

If you take too much mefenamic acid capsules, call your healthcare provider or Poison Help Line at 1-800-222-1222, or go to the nearest hospital emergency room right away.

What are the possible side effects of mefenamic acid capsules? Mefenamic acid capsules may cause serious side effects, including:
S ee "What is the most important information I should know about mefenamic acid capsules, and medicines called nonsteroidal anti-inflammatory drugs (NSAIDs)?"

- liver problems including liver failure
- heart failure
- increase in blood potassium level (hyperkalemia)
- serious skin reactions, including life-threatening skin reactions
- new or worse high blood pressure
- kidney problem including kidney failure
- life-threatening allergic reactions
- asthma attacks in people who have asthma
- low red blood cells (anemia)

Other side effects of mefenamic acid capsules include : stomach pain, constipation, diarrhea, indigestion, gas, heartburn, nausea, vomiting, dizziness, swelling, increased liver enzyme levels, headaches, itching, rashes, and ringing in the ear.
Get emergency help right away if you get any of the following symptoms:

- shortness of breath or trouble breathing
- chest pain
- weakness in one part or side of your body
- slurred speech
- swelling of the face or throat

Stop taking m efenamic acid capsules and call your healthcare provider right away if you get any of the following symptoms:

- nausea
- more tired or weaker than usual
- diarrhea
- itching
- your skin or eyes look yellow
- indigestion or stomach pain
- vomit blood
- there is blood in the bowel movement or it is black and sticky like tar
- unusual weight gain
- skin rash or blisters with fever
- swelling of the arms, legs, hands, and feet
- flu-like symptoms

These are not all of the possible side effects of mefenamic acid capsules.
Call your doctor for medical advice about side effects. You may report side effects to FDA at 1-800-FDA-1088 or Lupin Pharmaceuticals, Inc at 1-800-399-2561.

Other information about NSAIDs

- Aspirin is an NSAID medicine but it does not increase the chance of a heart attack. Aspirin can cause bleeding in the brain, stomach, and intestines. Aspirin can also cause ulcers in the stomach and intestines.
- Some NSAIDs are sold in lower doses without a prescription (over-the-counter). Talk to your healthcare provider before using over-the-counter NSAID.

How should I store mefenamic acid capsules?

- Store mefenamic acid capsules at room temperature at 25°C (77°F).

Keep m efenamic acid capsules and all medicines out of the reach of children.

General information about the safe and effective use of mefenamic acid capsules.
Medicines are sometimes prescribed for purposes other than those listed in a Medication Guide. Do not use mefenamic acid capsules for a condition for which it was not prescribed. Do not give mefenamic acid capsules to other people, even if they have the same symptoms that you have. It may harm them. You can ask your pharmacist or healthcare provider for information about mefenamic acid capsules that is written for health professionals.

What are the ingredients in mefenamic acid capsules?
Active ingredient: mefenamic acid
Inactive ingredient : lactose monohydrate and magnesium stearate. The capsule shell contains gelatin, sodium lauryl sulfate, titanium dioxide, D&C yellow No. 10, FD&C yellow No. 6 and FD&C red No. 3.
LUPIN and the are registered trademarks of Lupin Pharmaceuticals, Inc.
Manufactured for:
Lupin Pharmaceuticals, Inc.
Naples, FL 34108
United States
Manufactured by:
Lupin Limited
Goa 403 722
INDIA

This Medication Guide has been approved by the U.S. Food and Drug Administration.

Revised: 02/2026 ID: 282952

PACKAGE LABEL.PRINCIPAL DISPLAY PANEL

MEFENAMIC ACID CAPSULES USP

Rx ONLY

250 mg

NDC No.- 68180-185-06

30s Pack

Image 1